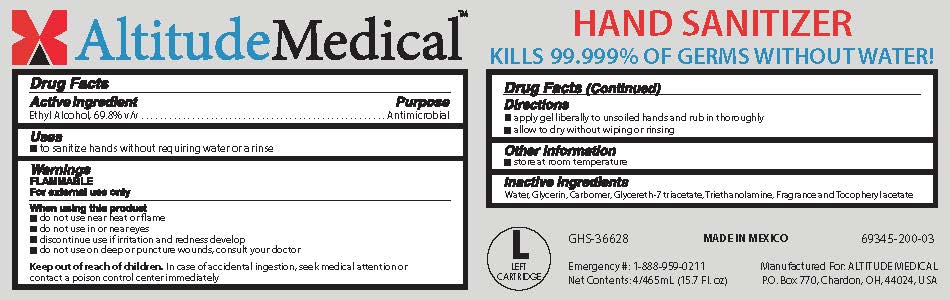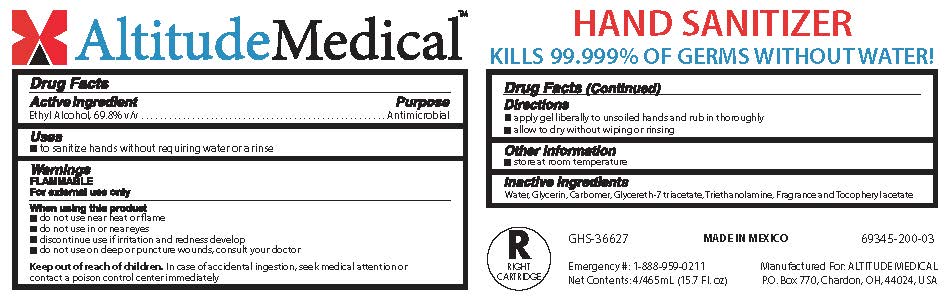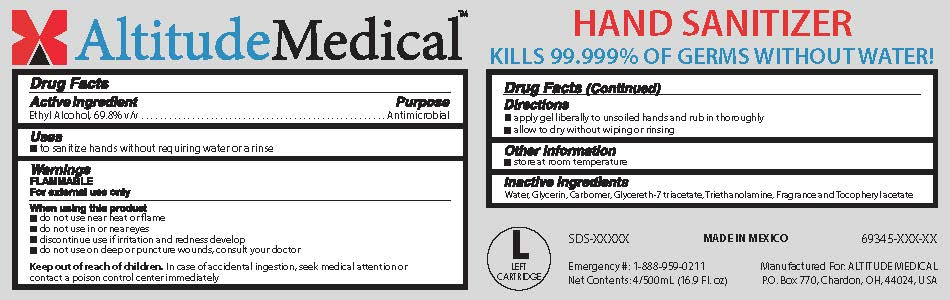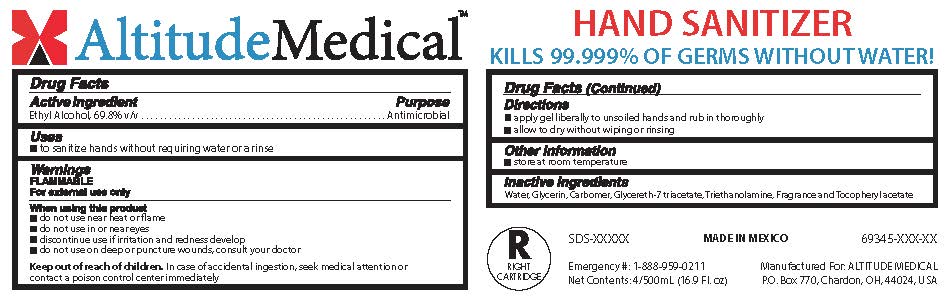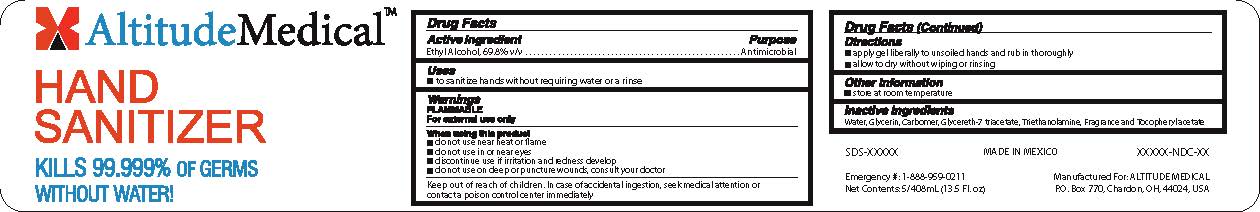 DRUG LABEL: Altitude Medical Hand Sanitizer
NDC: 69345-200 | Form: GEL
Manufacturer: Altitude Medical
Category: otc | Type: HUMAN OTC DRUG LABEL
Date: 20181018

ACTIVE INGREDIENTS: ALCOHOL 69.8 mL/100 mL
INACTIVE INGREDIENTS: WATER; glycerin; CARBOMER INTERPOLYMER TYPE A (ALLYL SUCROSE CROSSLINKED); GLYCERETH-7 TRIACETATE; TROLAMINE; .ALPHA.-TOCOPHEROL, D-

Drug Facts

Active ingredient

Ethyl alcohol, 69.8% v/v

Purpose

Antimicrobial

Uses

- Sanitize hands without requiring water or a rinse

Warnings

Flammable

For external use only

When using this product

- Do not use near heat or flame
- Do not use in or near eyes
- Discontinue use if irritation and redness develop
- Do not use on deep or puncture wounds, consult your doctor

Keep out of reach of children.

In case of accidental ingestion, seek medical attention or contact a poison control center immediately.

Directions

- apply gel liberally to unsoiled hands and rub in thoroughly
- allow to dry without wiping or rinsing

Other information

- Store at room temperature

Inactive ingredients

Water, glycerin, carbomer, glycereth-7 triacetate, triethanolamine, fragrance and tocopherol acetate.

PACKAGE LABEL

AltitudeMedical
Hand Sanitizer
Kills 99.999% of germs without water!
Net Contents 5/408mL (13.5 Fl oz)
Emergency #
1-888-959-0211

PACKAGE LABEL

AltitudeMedical™
Hand Sanitizer
Kills 99.999% of germs without water!
Net Contents 4/500mL (16.9 Fl oz)
Emergency # : 1-888-959-0211

PACKAGE LABEL

AltitudeMedical™
Hand Sanitizer
Kills 99.999% of germs without water!
Net Contents 4/465mL (15.7 Fl oz)
Emergency # : 1-888-959-0211